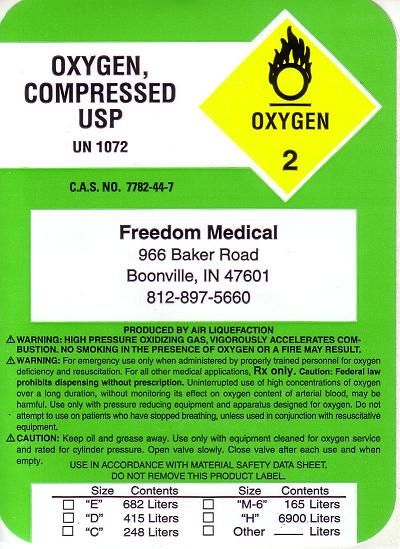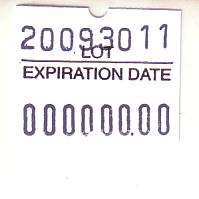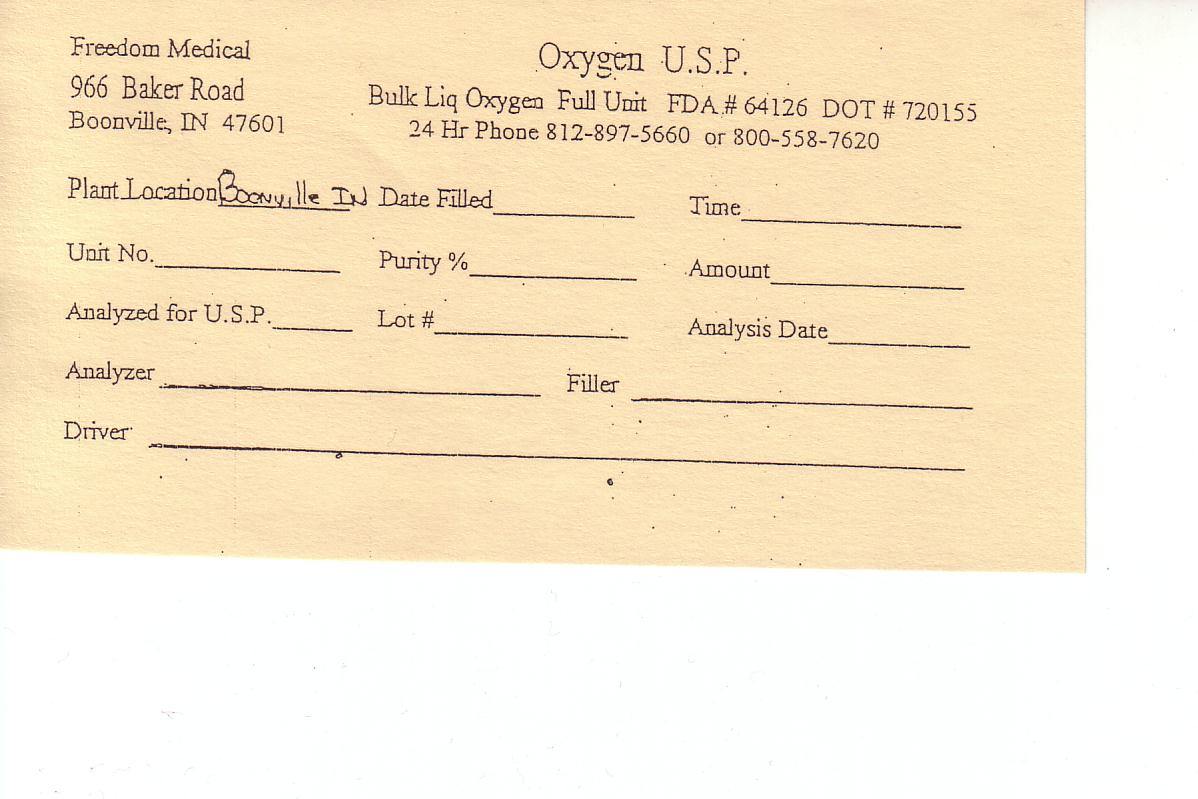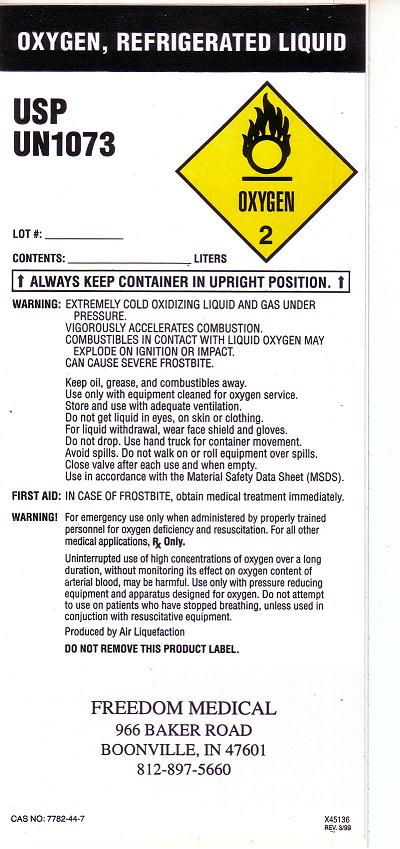 DRUG LABEL: Oxygen
NDC: 64126-1234 | Form: GAS
Manufacturer: Freedom Medical 
Category: prescription | Type: HUMAN PRESCRIPTION DRUG LABEL
Date: 20091030

ACTIVE INGREDIENTS: Oxygen 99 L/100 L

Oxygen